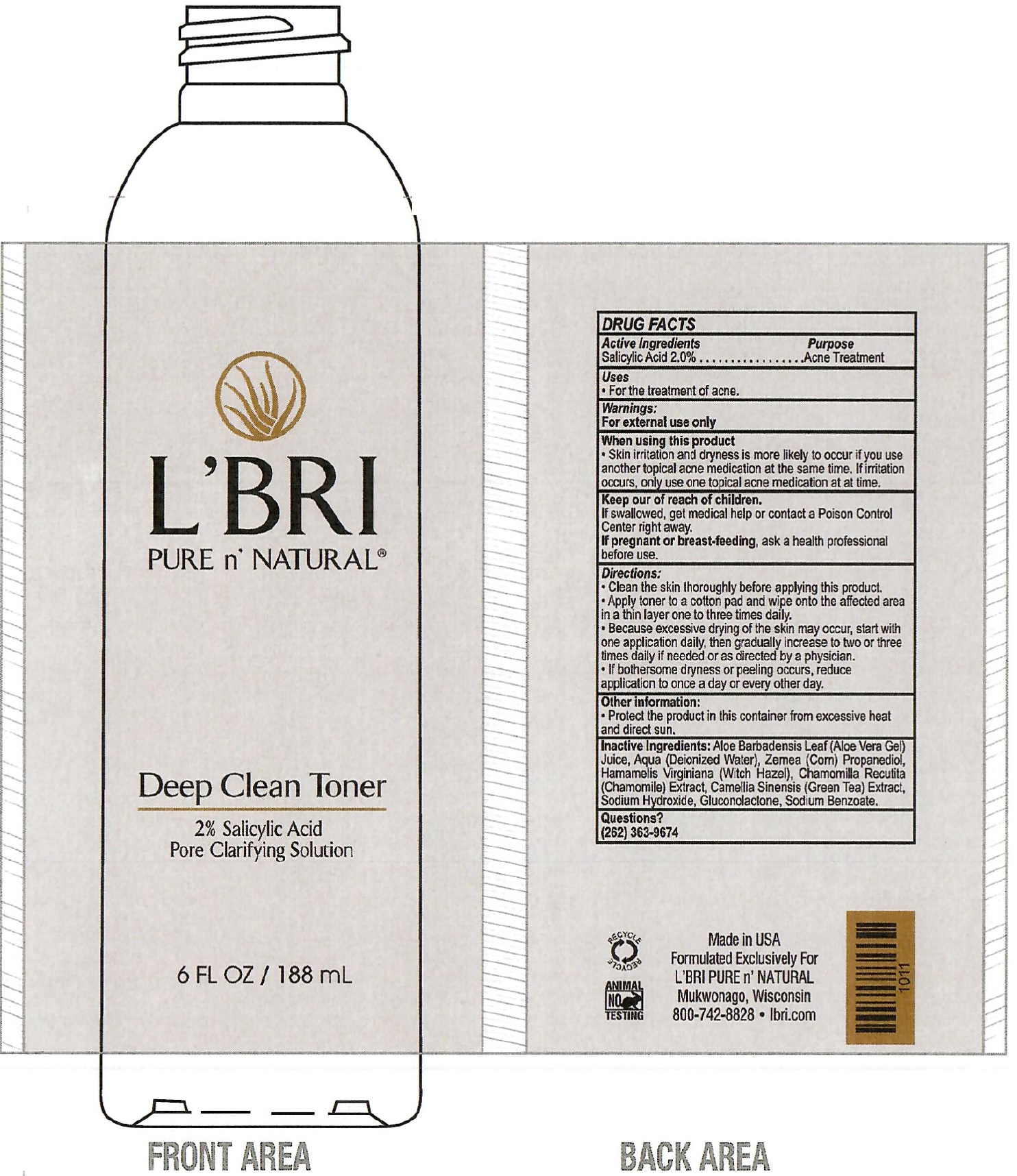 DRUG LABEL: L BRI Pure n Natural Deep Clean Toner
NDC: 71238-218 | Form: LIQUID
Manufacturer: L'BRI HEALTH AND BEAUTY INC
Category: otc | Type: HUMAN OTC DRUG LABEL
Date: 20231111

ACTIVE INGREDIENTS: SALICYLIC ACID 20 mg/1 mL
INACTIVE INGREDIENTS: ALOE VERA LEAF; WATER; CORN; WITCH HAZEL; CHAMOMILE; GREEN TEA LEAF; SODIUM HYDROXIDE; GLUCONOLACTONE; SODIUM BENZOATE

L'BRI Pure n' Natural Deep Clean Toner

Active Ingredients

Salicylic Acid 2.0%

Purpose

Acne Treatment

Uses

- For the treatment of acne.

Warnings:

For external use only

When using this product

- Skin irritation and dryness is more likely to occur if you use another topical acne medication at the same time. If irritation occurs, only use one topical acne medication at at time.

Keep out of reach of children.

If swallowed, get medical help or contact a Poison Control Center right away.

If pregnant or breast-feeding,

ask a health professional before use.

Directions:

- Clean the skin thoroughly before applying this product.
- Apply toner to a cotton pad and wipe onto the affected area in a thin layer one to three times daily.
- Because excessive drying of the skin may occur, start with one application daily, then gradully increase to two or three times daily if needed or as directed by a physician.
- If bothersome dryness or peeling occurs, reduce application to once a day or every other day.

Other information:

Protect the product in this container from excessive heat and direct sun.

Inactive Ingredients:

Aloe Barbadensis Leaf (Aloe Vera Gel) Juice, Aqua (Deionized Water), Zemea (Corn) Propanediol, Hamamelis Virginiana (Witch Hazel), Chamomilla Recutita (Chamomile) Extract, Camellia Sinensis (Green Tea) Extract, Sodium Hydroxide, Gluconolactone, Sodium Benzoate.

Questions?

(262) 363-9674